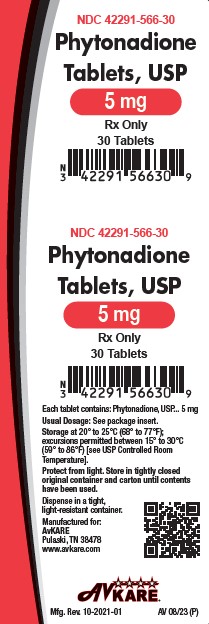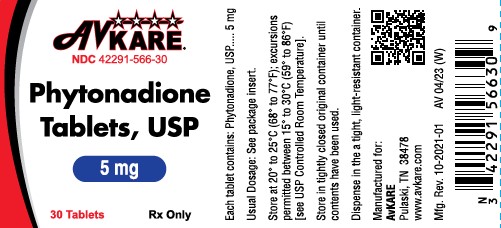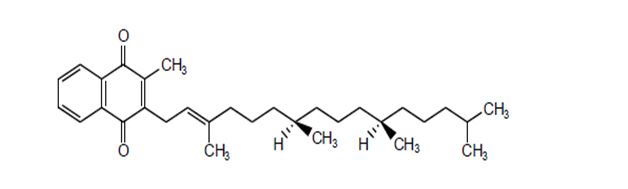 DRUG LABEL: Phytonadione
NDC: 42291-566 | Form: TABLET
Manufacturer: AvKARE
Category: prescription | Type: HUMAN PRESCRIPTION DRUG LABEL
Date: 20260115

ACTIVE INGREDIENTS: PHYTONADIONE 5 mg/1 1
INACTIVE INGREDIENTS: ACACIELLA ANGUSTISSIMA BARK; ANHYDROUS DIBASIC CALCIUM PHOSPHATE; LACTOSE MONOHYDRATE; MAGNESIUM STEARATE; SILICON DIOXIDE; STARCH, CORN; TALC

HIGHLIGHTS OF PRESCRIBING INFORMATION

Phytonadione Tablets, USP
These highlights do not include all the information needed to use PHYTONADIONE TABLETS safely and effectively. See full prescribing information for PHYTONADIONE TABLETS.
Initial U.S. Approval: 1955

1 INDICATIONS AND USAGE

Phytonadione is a vitamin K replacement indicated for the treatment of adults with the following coagulation disorders which are due to faulty formation of factors II, VII, IX and X when caused by vitamin K deficiency or interference with vitamin K activity:

- Anticoagulant-induced prothrombin deficiency caused by coumarin or indanedione derivatives. (1)
- Hypoprothrombinemia secondary to antibacterial therapy. (1)
- Hypoprothrombinemia secondary to factors limiting absorption or synthesis of vitamin K, e.g., obstructive jaundice, biliary fistula, sprue, ulcerative colitis, celiac disease, intestinal resection, cystic fibrosis of the pancreas, and regional enteritis. (1)
- Other drug-induced hypoprothrombinemia where it is definitively shown that the result is due to interference with vitamin K metabolism, e.g., salicylates. (1)

2 DOSAGE AND ADMINISTRATION

- Anticoagulant-Induced Prothrombin Deficiency: 2.5 mg to 10 mg or up to 25 mg. (2.2)
- Hypoprothrombinemia Due to Other Causes: 2.5 mg to 25 mg or more. (2.2)
- Must be given with bile salts when endogenous supply of bile to gastrointestinal track is deficient. (2.1)

3 DOSAGE FORMS AND STRENGTHS

Tablets: 5 mg (3)

4 CONTRAINDICATIONS

Hypersensitivity to any component of this medication. (4)

6 ADVERSE REACTIONS

Most common adverse reactions are transient “flushing sensations”, “peculiar” sensations of taste and instances of dizziness, rapid and weak pulse, profuse sweating, brief hypotension, dyspnea, and cyanosis. (6)

To report SUSPECTED ADVERSE REACTIONS, contact AvKARE at 1-855-361-3993 or FDA at 1-800-FDA-1088 or www.fda.gov/medwatch.

7 DRUG INTERACTIONS

Anticoagulants: May induce temporary resistance to prothrombin-depressing anticoagulants. (7)

FULL PRESCRIBING INFORMATION

1 INDICATIONS AND USAGE

Phytonadione tablets are indicated for the treatment of adults with the following coagulation disorders which are due to faulty formation of factors II, VII, IX and X when caused by vitamin K deficiency or interference with vitamin K activity.

- Anticoagulant-induced hypoprothrombinemia caused by coumarin or indanedione derivatives.
- Hypoprothrombinemia secondary to antibacterial therapy.
- Hypoprothrombinemia secondary to factors limiting absorpsion or synthesis of vitamin K, e.g., obstructive jaundice, biliary fistula, sprue, ulcerative colitis, celiac disease, intestinal resection, cystic fibrosis of the pancrease, and regional enteritis.
- Other drug-induced hypoprothrombinemia where it is definitely shown that the result is due to interference with vitamin K metabolism, e.g., salicylates.

2 DOSAGE AND ADMINISTRATION

2.1 Dosing Considerations

Avoid the oral route when the clinical disorder would prevent proper absorption. Bile salts must be given with the tablets when the endogenous supply of bile to the gastrointestinal tract is deficient. The coagulant effects of phytonadione tablets are not immediate; improvement of international normalized ratio (INR) may take 1 to 8 hours. Interim use of whole blood or component therapy may also be necessary if bleeding is severe.

Phytonadione tablets will not counteract the anticoagulant action of heparin.

When phytonadione tablets are used to correct excessive anticoagulant-induced hypoprothrombinemia, anticoagulant therapy still being indicated, the patient is again faced with the clotting hazards existing prior to starting the anticoagulant therapy. Phytonadione tablets are not a clotting agent, but overzealous therapy with vitamin K1 may restore conditions which originally permitted thromboembolic phenomena. Dosage should be kept as low as possible, and prothrombin time should be checked regularly as clinical conditions indicate.

2.2 Recommended Dosage

Anticoagulant-Induced Prothrombin Deficiency in Adults

The recommended dose to correct excessively prolonged prothrombin times caused by oral anticoagulant therapy is, 2.5 mg to 10 mg or up to 25 mg initially. In some instances 50 mg may be required. Frequency and amount of subsequent doses should be determined by prothrombin time response or clinical condition. If, in 12 to 48 hours after oral administration, the prothrombin time has not been shortened satisfactorily, repeat the dose.

Repeated large doses of phytonadione tablets are not warranted in liver disease if the response to initial use of the vitamin is unsatisfactory. Failure to respond to phytonadione may indicate a congenital coagulation defect or that the condition being treated is unresponsive to vitamin K.

Hypoprothrombinemia Due to Other Causes in Adults

If possible, discontinuation or reduction of the dosage of drugs interfering with coagulation mechanisms (such as salicylates, antibiotics) is suggested as an alternative to administering concurrent phytonadione tablets. The severity of the coagulation disorder should determine whether the immediate administration of phytonadione tablets are required in addition to discontinuation or reduction of interfering drugs.

The recommended dose is 2.5 mg to 25 mg or more (sometimes up to 50 mg). Evaluate INR after 6 to 8 hours, and repeat dose if INR remains prolonged. Modify subsequent dosage (amount and frequency) based upon the INR or clinical condition.

3 DOSAGE FORMS AND STRENGTHS

Phytonadione tablets USP, 5 mg are light yellow to yellow colored, round, scored tablets, debossed with “AA” and “05” on either side of scoring and plain on the other side.

4 CONTRAINDICATIONS

Phytonadione tablets are contraindicated in patients with a history of a hypersensitivity reaction to phytonadione or inactive ingredients [see Description (11)] .

6 ADVERSE REACTIONS

The following adverse reactions associated with the use of parenteral phytonadione were identified in clinical studies or post-marketing reports. Because some of these reactions were reported voluntarily from a population of uncertain size, it is not always possible to reliably estimate their frequency or establish a causal relationship to drug exposure.

Severe hypersensitivity reactions, including anaphylactoid reactions and deaths, have been reported following parenteral administration. The majority of these reported events occurred following intravenous administration.

Transient “flushing sensations” and “peculiar” sensations of taste have been observed with parenteral phytonadione, as well as instances of dizziness, rapid and weak pulse, profuse sweating, brief hypotension, dyspnea, and cyanosis.

Hyperbilirubinemia has been observed in the newborn following administration of parenteral phytonadione. This has occurred primarily with doses above those recommended.

To report SUSPECTED ADVERSE REACTIONS, contact AvKARE at 1-855-361-3993 or FDA at 1-800-FDA-1088 or www.fda.gov/medwatch.

7 DRUG INTERACTIONS

Anticoagulants

Phytonadione may induce temporary resistance to prothrombin-depressing anticoagulants, especially when larger doses of phytonadione are used. Should this occur, higher doses of anticoagulant therapy may be needed when resuming anticoagulant therapy or a change in therapy to a different class of anticoagulant may be necessary (i.e., heparin sodium).

Phytonadione does not affect the anticoagulant action of heparin.

8 USE IN SPECIFIC POPULATIONS

8.1 Pregnancy

Risk Summary

Published studies with the use of phytonadione during pregnancy have not reported a clear association with phytonadione and adverse developmental outcomes [see Data]. There are maternal and fetal risks associated with vitamin K deficiency during pregnancy [see Clinical Considerations]. Animal reproduction studies have not been conducted with phytonadione.

The estimated background risk for the indicated population is unknown. All pregnancies have a background risk of birth defect, loss or other adverse outcomes. In the U.S. general population, the estimated background risk of major birth defects and miscarriage in clinically recognized pregnancies is 2% to 4% and 15% to 20%, respectively.

Clinical Considerations

Disease-associated maternal and/or embryo/fetal risk

Pregnant women with vitamin K deficiency hypoprothrombinemia may be at increased risk for bleeding diatheses during pregnancy and hemorrhagic events at delivery. Subclinical vitamin K deficiency during pregnancy has been implicated in rare cases of fetal intracranial hemorrhage.

Data

Human Data

Phytonadione has been measured in cord blood of infants whose mothers were treated with phytonadione during pregnancy in concentrations lower than seen in maternal plasma. Administration of vitamin K1 to pregnant women shortly before delivery increased both maternal and cord blood concentrations. Published data do not report a clear association with phytonadione and adverse maternal or fetal outcomes when used during pregnancy. However, these studies cannot definitively establish the absence of any risk because of methodologic limitations including small sample size and lack of blinding.

Animal Data

In pregnant rats receiving vitamin K1 orally, fetal plasma and liver concentrations increased following administration, supporting placental transfer.

8.2 Lactation

Risk Summary

Phytonadione is present in breastmilk. There are no data on the effects of phytonadione on the breastfed child or on milk production. The developmental and health benefits of breastfeeding should be considered along with the clinical need for phytonadione and any potential adverse effects on the breastfed child from phytonadione or from the underlying maternal condition.

8.4 Pediatric Use

Safety and effectiveness in pediatric patients have not been established with phytonadione. Hemolysis, jaundice, and hyperbilirubinemia in newborns, particularly in premature infants, have been reported with vitamin K.

8.5 Geriatric Use

Clinical studies of phytonadione did not include sufficient numbers of subjects aged 65 and over to determine whether they respond differently from younger subjects. Other reported clinical experience has not identified differences in responses between the elderly and younger patients. In general, dose selection for an elderly patient should be cautious, usually starting at the low end of the dosing range, reflecting the greater frequency of decreased hepatic, renal, or cardiac function, and of concomitant disease or other drug therapy.

11 DESCRIPTION

Phytonadione is a vitamin K replacement, which is a clear, yellow to amber, very viscous, odorless or practically odourless liquid. It is soluble in dehydrated alcohol, benzene, chloroform and ether; slightly soluble in alcohol (96%) and insoluble in water. It has a molecular weight of 450.70 g/mol.

Phytonadione is 1,4-Naphthalenedione, 2-methyl-3-(3,7,11,15-tetramethyl-2-hexadecenyl)-,[R-[R*,R*-(E)]]. Its molecular formula is C31H46O2and its structural formula is:

Phytonadione tablets, USP for oral administration contain 5 mg of phytonadione, USP and are light yellow to yellow colored, round, scored tablets, debossed with “AA” and “05” on either side of scoring and plain on the other side. Inactive ingredients are acacia, anhydrous dibasic calcium phosphate, colloidal silicon dioxide, lactose monohydrate, magnesium stearate, pregelatinized starch, and talc.

12 CLINICAL PHARMACOLOGY

12.1 Mechanism of Action

Phytonadione tablets possess the same type and degree of activity as does naturally-occurring vitamin K, which is necessary for the production via the liver of active prothrombin (factor II), proconvertin (factor VII), plasma thromboplastin component (factor IX), and Stuart factor (factor X). The prothrombin test is sensitive to the levels of three of these four factors – II, VII, and X. Vitamin K is an essential cofactor for a microsomal enzyme that catalyzes the posttranslational carboxylation of multiple, specific, peptide-bound glutamic acid residues in inactive hepatic precursors of factors II, VII, IX, and X. The resulting gamma-carboxyglutamic acid residues convert the precursors into active coagulation factors that are subsequently secreted by liver cells into the blood.

In normal animals and humans, phytonadione is virtually devoid of pharmacodynamic activity. However, in animals and humans deficient in vitamin K, the pharmacological action of vitamin K is related to its normal physiological function, that is, to promote the hepatic biosynthesis of vitamin K-dependent clotting factors.

12.2 Pharmacodynamics

Phytonadione tablets generally exert their effect within 6 to 10 hours.

12.3 Pharmacokinetics

Absorption

Oral phytonadione is adequately absorbed from the gastrointestinal tract only if bile salts are present.

Distribution

After absorption, phytonadione is initially concentrated in the liver, but the concentration declines rapidly. Very little vitamin K accumulates in tissues.

Elimination

Little is known about the metabolic fate of vitamin K. Almost no free unmetabolized vitamin K appears in bile or urine.

13 NONCLINICAL TOXICOLOGY

13.1 Carcinogenesis, Mutagenesis, Impairment of Fertility

Studies of carcinogenicity or impairment of fertility have not been performed with phytonadione. Phytonadione at concentrations up to 2,000 mcg/plate, with or without metabolic activation, was negative in the Ames microbial mutagen test.

16 HOW SUPPLIED/STORAGE AND HANDLING

Phytonadione Tablets USP, 5 mg are supplied as light yellow to yellow colored, round, scored tablets, debossed with “AA” and “05” on either side of scoring and plain on the other side.

They are available as follows:

Bottles of 30: NDC 42291-566-30

Storage

Store at 20° to 25°C (68° to 77°F); excursions permitted between 15° to 30°C (59° to 86°F) [see USP Controlled Room Temperature].

Always protect phytonadione tablets, USP from light.

Store in tightly closed original container and carton until contents have been used.

17 PATIENT COUNSELING INFORMATION

Vitamin K1 is fairly rapidly degraded by light; therefore, advise patients to always protect phytonadione tablets from light. Store phytonadione tablets in closed original carton until contents have been used [see How Supplied/Storage and Handling (16)] .

Manufactured for:

AvKARE

Pulaski, TN 38478

Mfg. Rev. 10-2021-01

AV 03/23 (W)